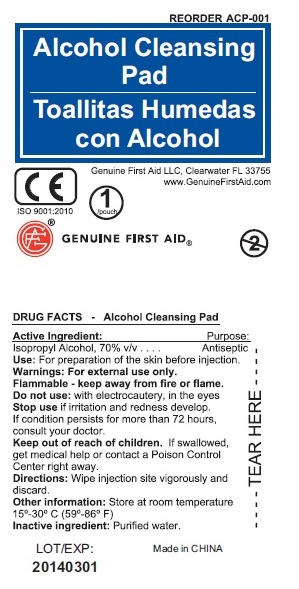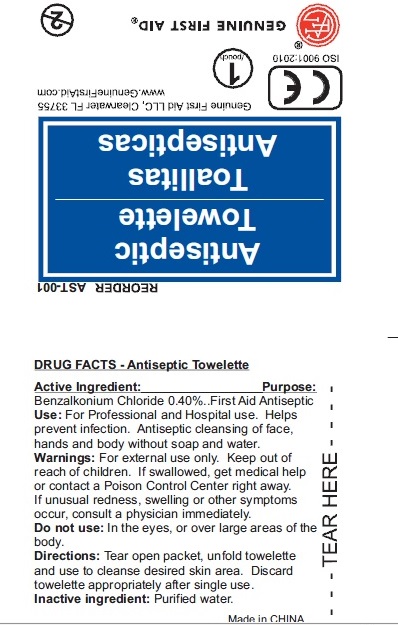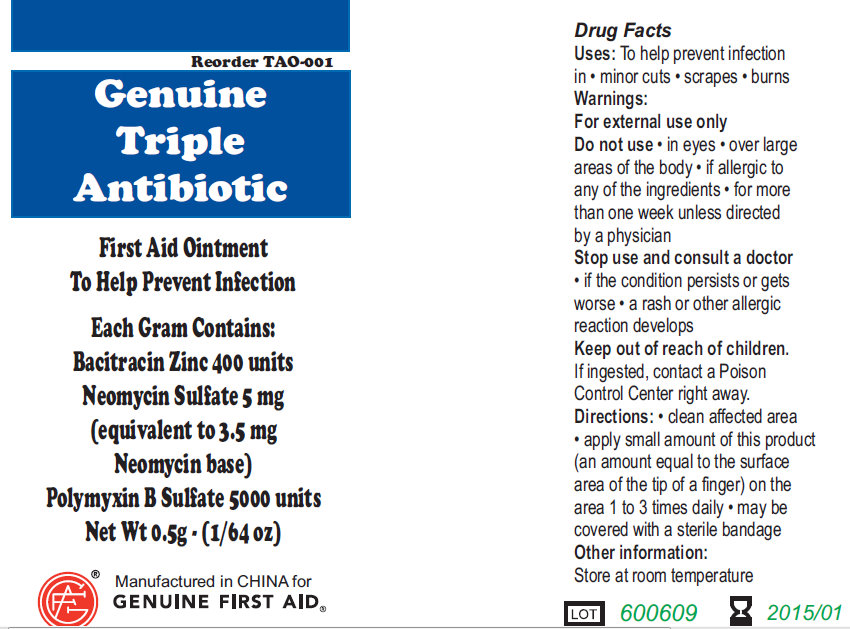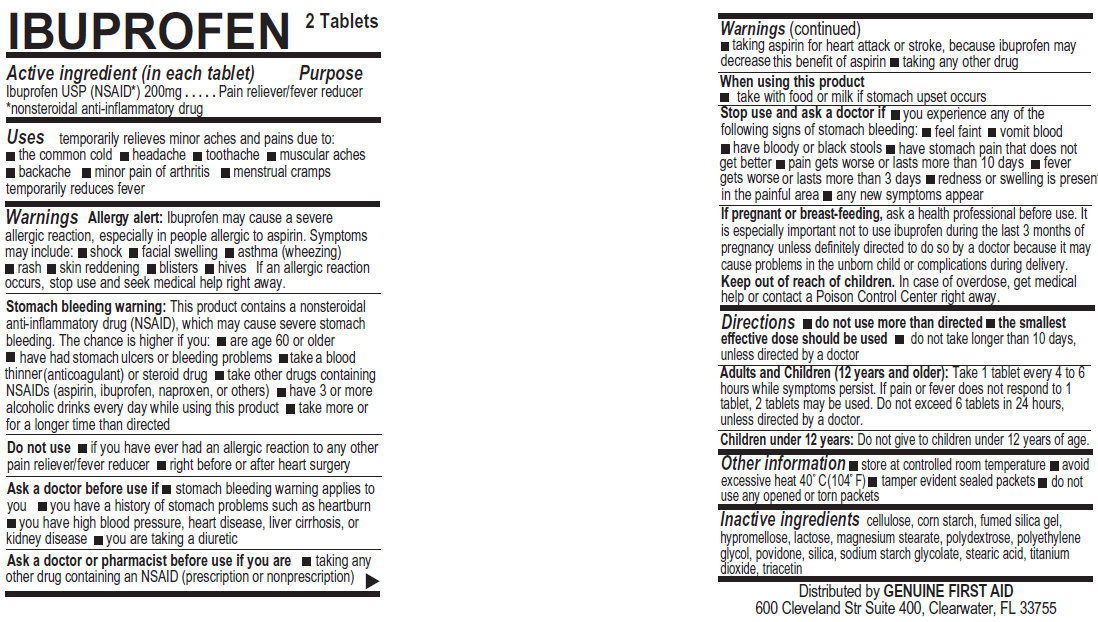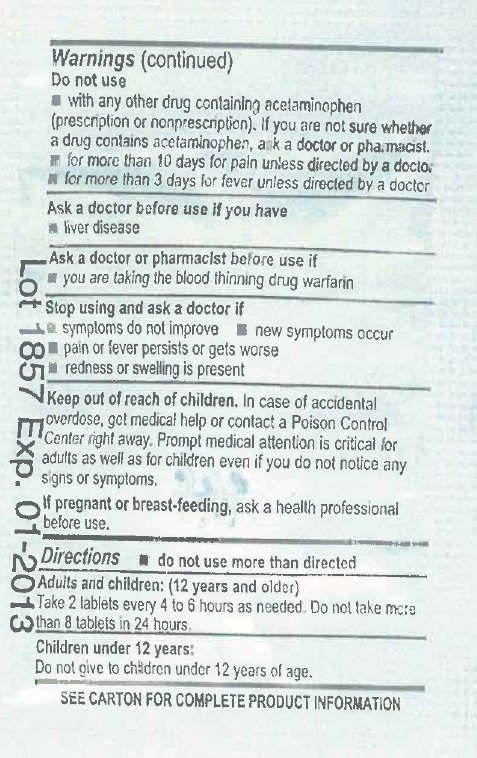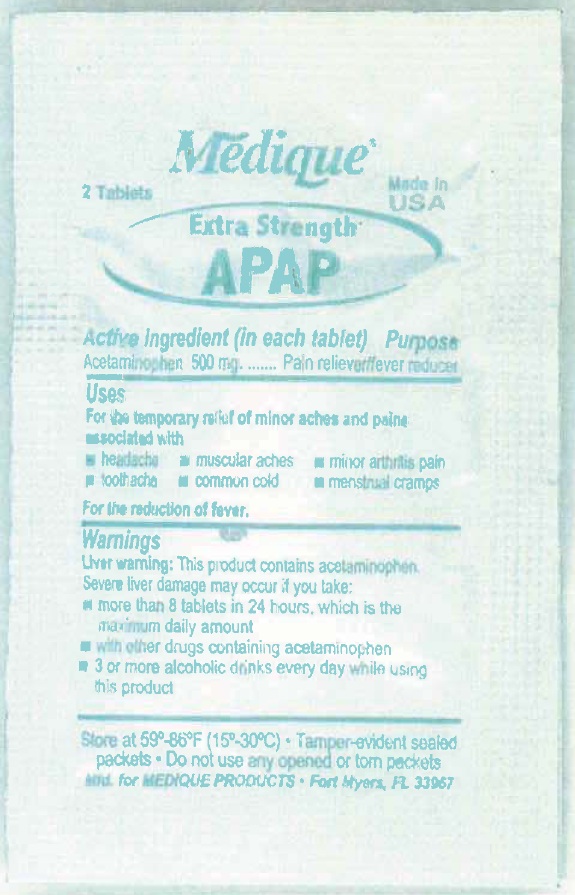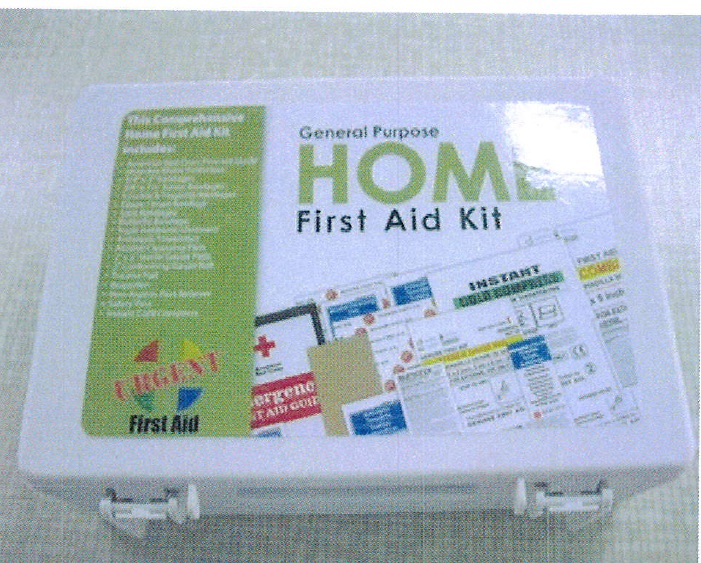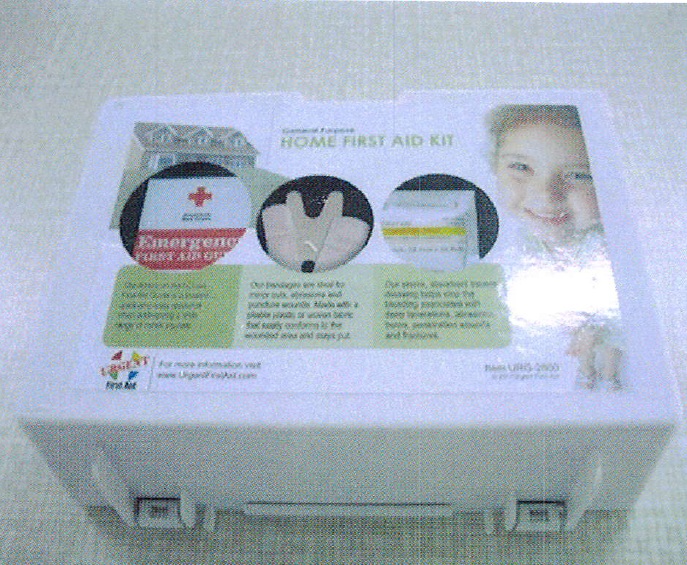 DRUG LABEL: Genuine First Aid - Home First Aid
NDC: 52124-1200 | Form: KIT | Route: TOPICAL
Manufacturer: Genuine First Aid, LLC
Category: otc | Type: HUMAN OTC DRUG LABEL
Date: 20110117

ACTIVE INGREDIENTS: BACITRACIN ZINC 400 [iU]/1 g; NEOMYCIN SULFATE 5 mg/1 g; POLYMYXIN B SULFATE 5000 [iU]/1 g; IBUPROFEN 200 mg/1 1; ACETAMINOPHEN 500 mg/1 1; BENZALKONIUM CHLORIDE 0.40 mL/100 mL; ISOPROPYL ALCOHOL 70 mL/100 mL
INACTIVE INGREDIENTS: WATER; POWDERED CELLULOSE; STARCH, CORN; HYPROMELLOSES; LACTOSE; MAGNESIUM STEARATE; POLYDEXTROSE; POLYETHYLENE GLYCOL; POVIDONE; SILICON DIOXIDE; STEARIC ACID; TITANIUM DIOXIDE; TRIACETIN; CROSPOVIDONE; HYDROXYPROPYL CELLULOSE; HYPROMELLOSES; MAGNESIUM STEARATE; CELLULOSE, MICROCRYSTALLINE; MINERAL OIL; POLYETHYLENE GLYCOL; POVIDONE; PROPYLENE GLYCOL; SILICON DIOXIDE; CARBOXYMETHYLCELLULOSE SODIUM; STEARIC ACID; TALC; TITANIUM DIOXIDE; TRIACETIN; WATER; WATER

Genuine First Aid Home First Aid Kit

Active Ingredient: Purpose
Isopropyl Alcohol, 70% v/v............... Antiseptic

PURPOSE

Use: For preparation of skin before injection.

Warnings: For external use only.

STORAGE AND HANDLING

Flammable - keep away from fire or flame
Store at room temperature 15-30 degree Celsius (59-86 degree Fahrenheit)

Do not use: with electrocautery, in the eyes.

Stop use if irritation and redness develop. If condition persists for more than 72 hours, consult your doctor.

Keep out of reach of children. If swallowed,
get medical help or contact a Poison Control
Center right away.

WHEN USING

Wipe Injection site vigorously and discard.

Inactive Ingredient: Purified water.

DESCRIPTION

LOT/EXP: Made in CHINA
20140301

PACKAGE LABEL

Alcohol Cleansing Pad
Genuine First Aid LLC, Clearwater FL 33755
www.GenuineFirstAid.com
1/pouch
GENUINE FIRST AID

Active Ingredient: .........Bacitracin Zinc 400 units

Neomycin Sulfate 5mg (equivalent to 3.5 mg Neomycin base)

Polymyxin B Sulfate 5000 units

PURPOSE

Uses: To help prevent infection in:
minor cuts; scrapes; burns

Warnings:

For external use only.

Do not use: in eyes; over large areas of the body;

If allergic to any of the ingredients; for more than one week unless directed by a physician.

Stop use and consult a doctor:

if the condition persists or gets worse; a rash or other allergic reaction develops

Keep out of reach of children.

If ingested, contact a Poison

Control Center right away.

WHEN USING

Directions: clean affected area; apply small amount of this product (an amount equal to the surface area of the tip of a finger) on the area 1 to 3 times daily; may be covered with a sterile bandage

Other information:

Store at room temperature.

PACKAGE LABEL

Genuine Triple Antibiotic

First Aid Ointment

To Help Prevent Infection

Each Gram Contains:

Bacitracin Zinc 400 units

Neomycin Sulfate 5 mg

(equivalent to 3.5 mg

Neomycin base)

Polymyxin B Sulfate 5000 units

Net Wt. 0.5g ; (1/64 oz)

Manufactured in CHINA for

GENUINE FIRST AID.

Active ingredient (in each tablet) Purpose

Ibuprofen USP (NSAID*) 200mg . . . . . . . . . . . .Pain reliever/fever reducer

*nonsteroidal anti-inflammatory drug

PURPOSE

Uses temporarily relieves minor aches and pains due to:
the common cold
headache
toothache
muscular aches
backache
minor pain of arthritis
menstrual cramps temporarily reduces fever

Warnings

Allergy alert: Ibuprofen may cause a severe allergic reaction, especially in people allergic to aspirin. Symptoms may include: shock, facial swelling, asthma (wheezing) rash, skin reddening, blisters, hives If an allergic reaction occurs, stop use and seek medical help right away.

Stomach bleeding warning: This product contains a nonsteroidal anti-inflammatory drug (NSAID), which may cause severe stomach
bleeding. The chance is higher if you: are age 60 or older, have had stomach ulcers or bleeding problems, take a blood thinner (anticoagulant) or steroid drug, take other drugs containing NSAIDs (aspirin, ibuprofen, naproxen, or others), have 3 or more alcoholic drinks every day while using this product, take more or for a longer time than directed

Do not use if you have ever had an allergic reaction to any other pain reliever/fever reducer, right before or after heart surgery.

Ask a doctor before use if stomach bleeding warning applies to you; you have a history of stomach problems such as heartburn; you have a high blood pressure, heart disease, liver cirrhosis, or kidney disease; you are taking a diuretic

Ask a doctor before use if you are:
taking any other drug containing NSAID (prescription or nonprescription); taking aspirin for heart attack or stroke, because Ibuprofen may decrease this benefit of aspirin; taking any other drug

When using this product:
take with food or milk if stomach upset occurs

Stop use and ask a doctor If:
you experience any of the following signs of stomach bleeding; feel faint; vomit blood; have bloody or black stools; have stomach pain that does get better; pain gets worse or lasts more than 10 days; fever gets worse or lasts more than 3 days; redness or swelling is present in the painful area; any new symptoms appear

PREGNANCY OR BREAST FEEDING

If pregnant or breast-feeding, ask a health professional before use. It is especially important not to use ibuprofen during the last 3 months of pregnancy unless definitely directed to do so by a doctor because it may cause problems in the unborn child or complications during delivery.

Keep out of reach of children. In case of overdose, get medical help or contact a Poison Control Center right away.

Directions:
do not use more than directed; the smallest effective dose should be used; do not take longer than 10 days, unless directed by a doctor.
Adults and Children (12 years and older): Take 1 tablet every 4 to 6 hours while symptoms persist. If pain or fever does not respond to 1 tablet, 2 tablets may be used. Do not exceed 6 tablets in 24 hours, unless directed by a doctor.
Children under 12 years: Do not give to children under 12 years of age.

Other information: Store at controlled room temperature; avoid excessive heat 40 degree Celsius (104 degree Fahrenheit); tamper evident sealed packets; do not use any opened or torn packets

INACTIVE INGREDIENT

Inactive ingredients: cellulose, corn starch, fumed silica gel, hypromellose, lactose, magnesium stearate, polydextrose, polyethylene glycol, povidone, silica, sodium starch glycolate, stearic acid, titanium dioxide, triacetin.

DESCRIPTION

Distributed by GENUINE FIRST AID
600 Cleveland Str Suite 400, Clearwater, FL 33755

PACKAGE LABEL

IBUPROFEN 2 Tablets

Active Ingredient (in each tablet) Purpose

Acetaminophen 500 mg............................... Pain Reliever / fever reducer

Purpose: Pain reliever, fever reducer

INDICATIONS AND USAGE

Uses for the temporary relief of minor aches and pains associated with
headache ; muscular aches ; minor arthritis pain ; toothache ; common cold ; menstrual cramps ; for the reduction of fever

Warnings

Liver Warning: This product contains acetaminophen. Sever liver damage may occur if you take: more than 8 tablets in 24 hours, which is the maximum daily amount; with other drugs containing acetaminophen; 3 or more alcoholic drinks every day while using this product.

Do not use: with any other drug containing acetaminophen (prescription or non prescription). If you are not sure whether a drug contains acetaminiophen, ask a doctor or phramacist.
for more than 10 days for pain unless directed by a doctor
for more than 3 days for fever unless directed by a doctor

Ask a doctor before use if you have liver disease

Ask a doctor or pharmacist before use if you are taking the blood thinning drug warfarin

Stop using and ask a doctor if
symptoms do not improve
new symptoms occur
pain or fever persists or gets worse
redness or swellign is present

Keep out of reach of children. In case of accidental overdose, get medical help or contact a Poison Control Center right away. Prompt medical attention is critical for adults as well as for children even if you do not notice any signs or symptoms

PREGNANCY OR BREAST FEEDING

If pregnant or breast-feeding, ask a health professional before use.

DOSAGE AND ADMINISTRATION

Adults and children: (12 years and older)
take 2 tablets every 4 to 6 hours as needed. Do not take more than 8 tablets in 24 hours.

Children under 12 years:
do not give to children under 12 years of age.

STORAGE AND HANDLING

Store at 59 - 86 degree Fahrenheit (15 - 30 degree Celsius); Tamper-evident sealed packets. do not use any opened or torn packets Mfd. for MEDIQUE PRODUCTS, FORT MYERS, FL 33967

INACTIVE INGREDIENT

Inactive Ingredients:Cellulose*, corn starch*, crospovidone*, hydroxypropyl cellulose*, hypromellose*, magnesium stearate*, microcrystalline cellulose*, mineral oil*, opadry clear*, polyethylene glycol*, polyvinylpyrrolidone*, povidone*, pregelatinized starch*, propylene glycol*, silicon dioxide*, sodium carboxymethylcellulose*, sodium starch glycolate*, starch 1500*, stearic acid, talc*, titanium dioxide*, triacetin*.

Active Ingredient: Purpose

Benzalkonium Chloride 0.40%.......... First Aid Antiseptic

PURPOSE

Use: For Professional and Hospital use. Helps prevent infection. Antiseptic cleansing of face, hands and body without soap and water.

WARNINGS

Warning: For external use only.

Keep out of reach of children: If swallowed, get medical help or contact a Poison Control Center right away.

Stop use if unusual redness, swelling or other symptoms occur. Consult a physician immediately.

Do not use in the eyes or over large areas of the body.

WHEN USING

Directions: Tear open packet, unfold towelette and use to cleanse desired skin area. Discard towelette appropriately after single use.

Inactive Ingredient: Purified water

DESCRIPTION

LOT/EXP: Made in CHINA

20130301

PACKAGE LABEL

Antiseptic Towelette

Genuine First Aid LLC, Clearwater FL 33755

www.GenuineFirstAid.com

1/pouch

GENUINE FIRST AID